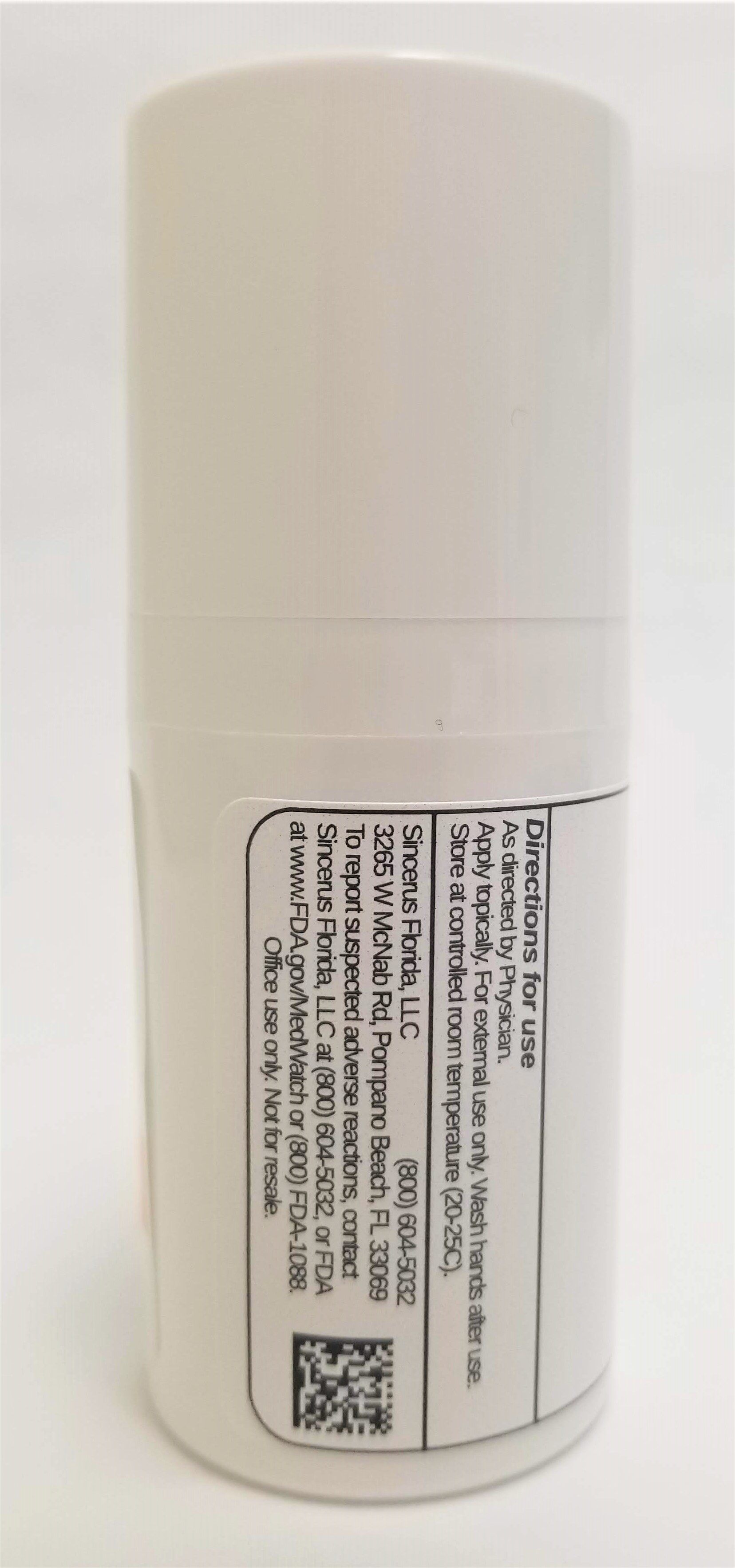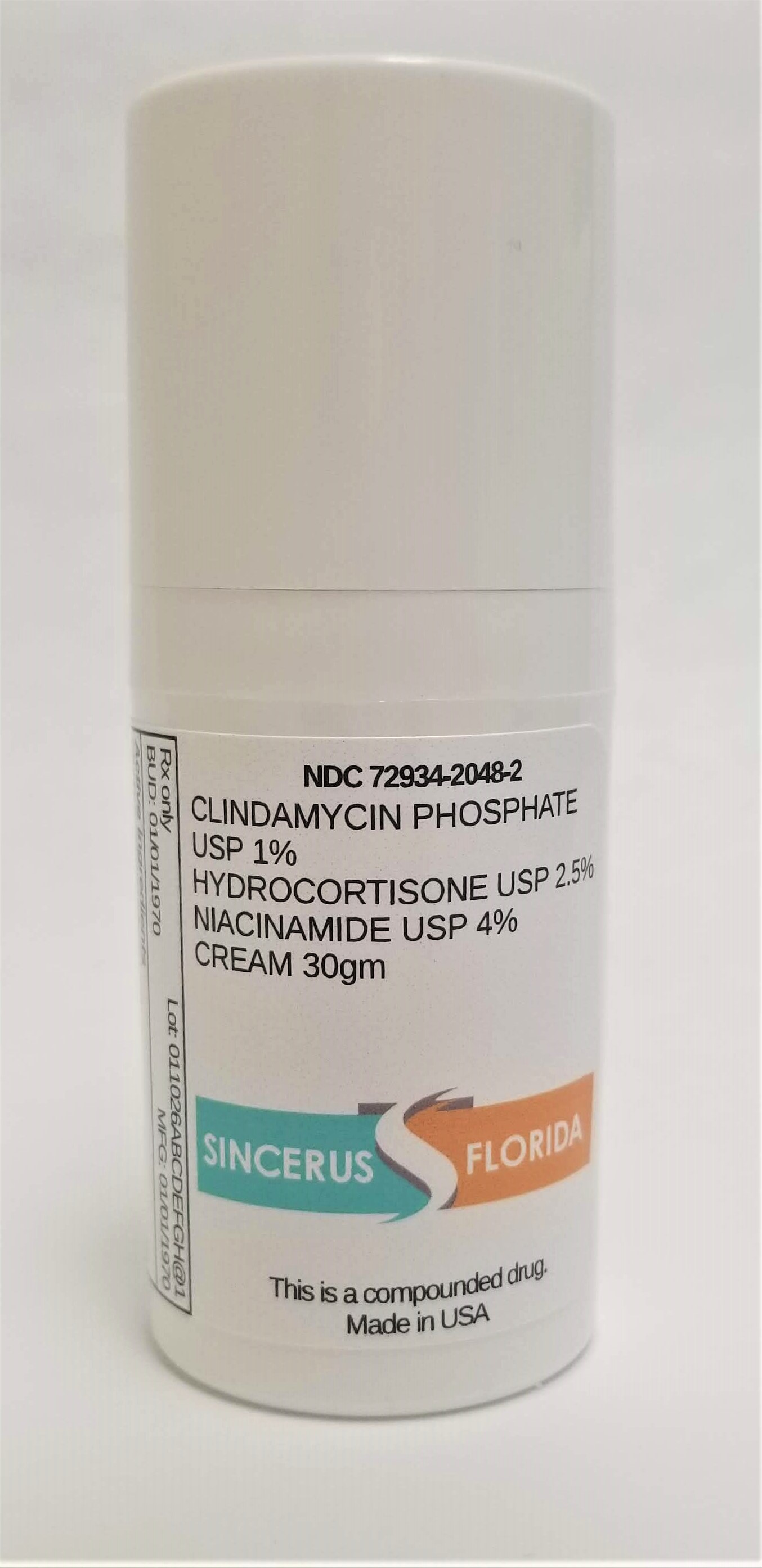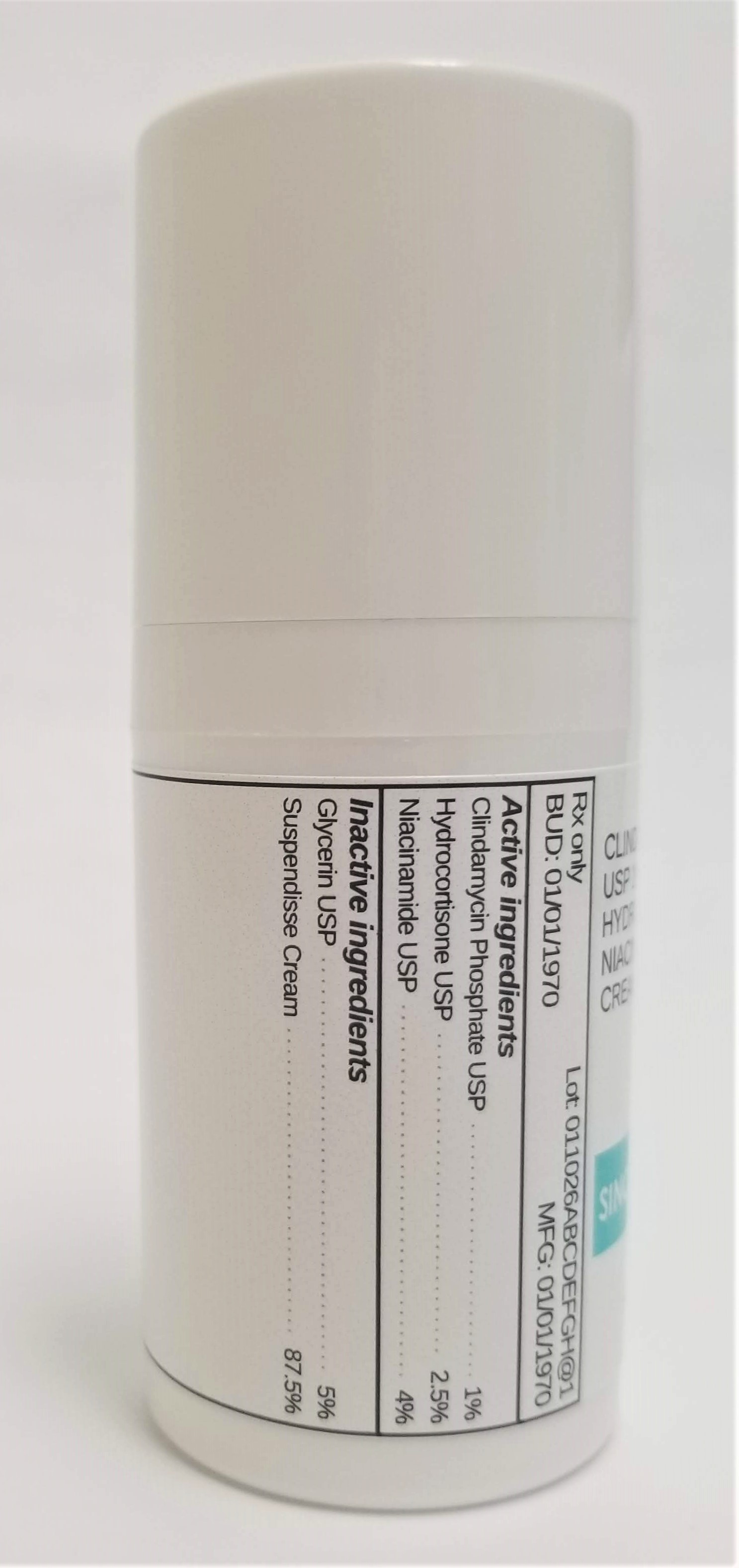 DRUG LABEL: CLINDAMYCIN 1% / HYDROCORTISONE 2.5% / NIACINAMIDE 4%
NDC: 72934-2048 | Form: CREAM
Manufacturer: Sincerus Florida, LLC
Category: prescription | Type: HUMAN PRESCRIPTION DRUG LABEL
Date: 20190509

ACTIVE INGREDIENTS: HYDROCORTISONE 2.5 g/100 g; NIACINAMIDE 4 g/100 g; CLINDAMYCIN PHOSPHATE 1 g/100 g

CLINDAMYCIN 1% / HYDROCORTISONE 2.5% / NIACINAMIDE 4%